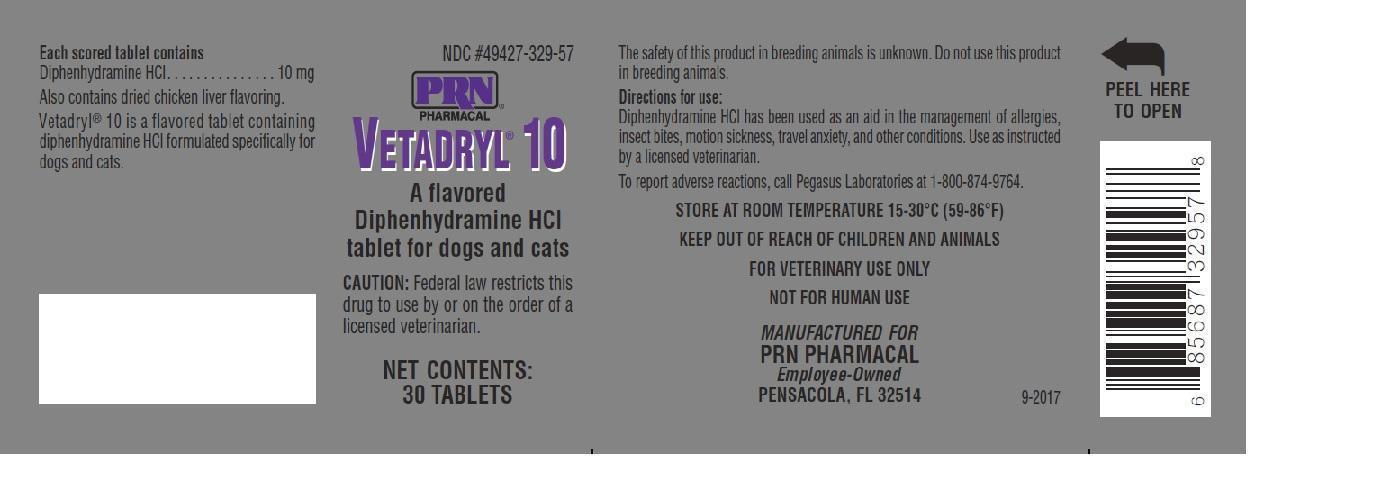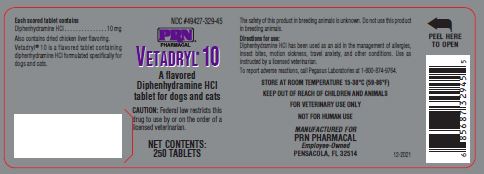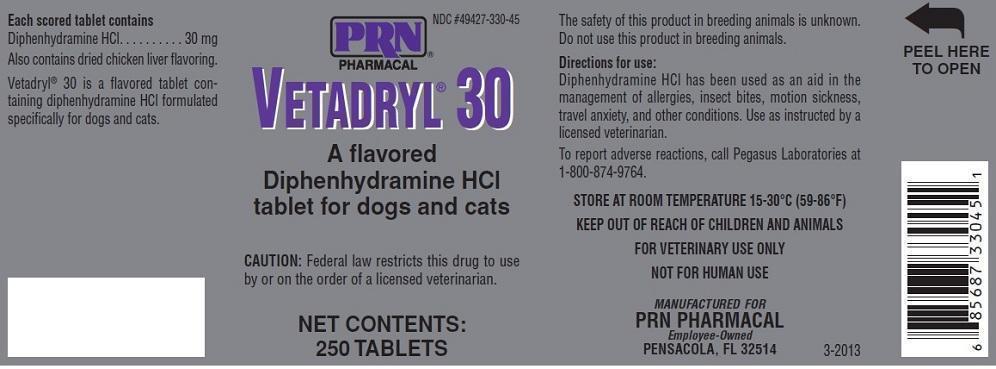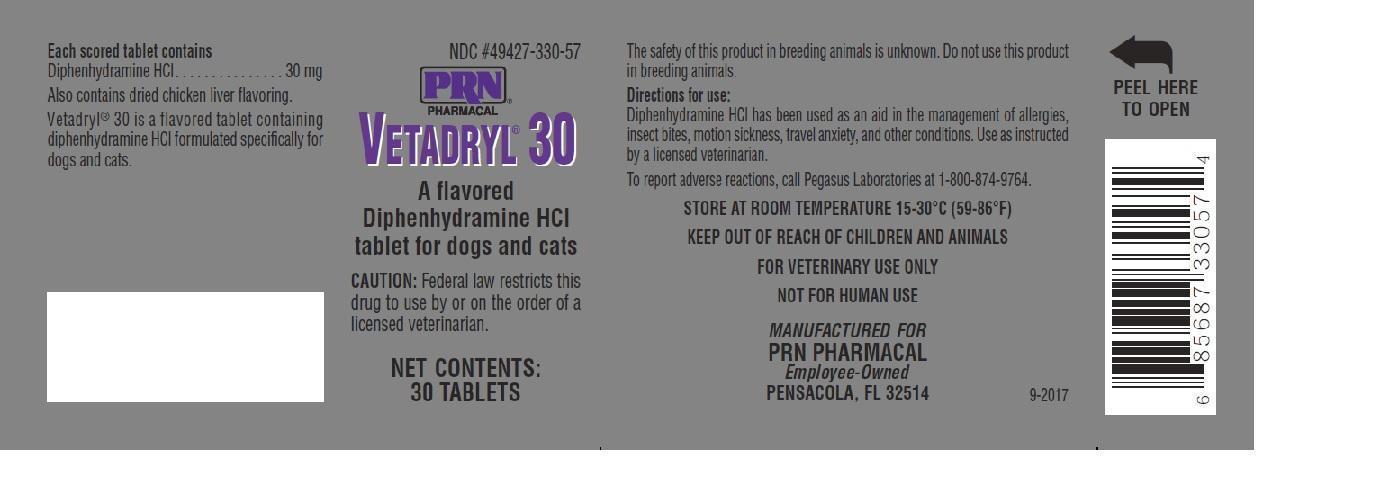 DRUG LABEL: Vetadryl 10
NDC: 49427-329 | Form: TABLET
Manufacturer: Pegasus Laboratories, Inc
Category: animal | Type: PRESCRIPTION ANIMAL DRUG LABEL
Date: 20241226

ACTIVE INGREDIENTS: DIPHENHYDRAMINE HYDROCHLORIDE     10 mg/1 1

Vetadryl 10/30 Tablets

Description:

Vetadryl 10/30 is a flavored tablet containing diphenhydramine HCl formulated specifically for dogs and cats.

Directions for use:

Diphenhydramine HCl has been used as an aid in the management of allergies, insect bites, motion sickness, travel anxiety, and other conditions. Use as instructed by a licensed veterinarian.

Dosage Information:

For Dogs
Indication | Dosage | Frequency
Motion sickness | 2-4mg/kg PO | every 8 hours
As an aid in allergy management | 2-4mg/kg PO | every 8-12 hours
As an aid in managing atopic dermatitis | 25-50mg (total dose) | three times daily
Travel anxiety | 2-4mg/kg PO | every 12 hours

For Cats
Indication | Dosage | Frequency
As an aid in allergy management | 2-4mg/kg PO | every 12-24 hours

Each scored tablet contains

Diphenhydramine HCl................10/30mg

Also contains dried chicken liver flavoring.

Storage:

STORE AT ROOM TEMPERATURE

15-30°C (59-86°F)

Caution:

Federal law restricts this drug to use by or on the order of a licensed veterinarian.

KEEP OUT OF REACH OF CHILDREN AND ANIMALS

FOR VETERINARY USE ONLY

NOT FOR HUMAN USE

The safety of this product in breeding animals is unknown. Do not use this product in breeding animals.

Adverse Reactions:

To report adverse reactions, call Pegasus Laboratories at 1-800-874-9764.

Overdose Information:

A diphenhydramine overdose can cause CNS stimulation (lethargy, somnolence), anti-cholinergic effects (dry mouth, urinary retention), and GI effects (diarrhea, vomiting, anorexia). This product may cause paradoxical excitement in cats. Contact your veterinarian if your animal experiences any of the above conditions after taking this product.

Principal Display Panel:

PRN PHARMACAL NDC #49427-329-45 or NDC #49427-330-45 or NDC #49427-329-57 or NDC #49427-330-57

VETADRYL 10/30

A flavored Diphenhydramine HCl

tablet for dogs and cats

CAUTION: Federal law restricts this drug to use by or on the order of a licensed veterinarian.

NET CONTENTS:

30/250 Tablets

Manufactured for

PRN PHARMACAL

Employee-Owned

PENSACOLA, FL. 32514